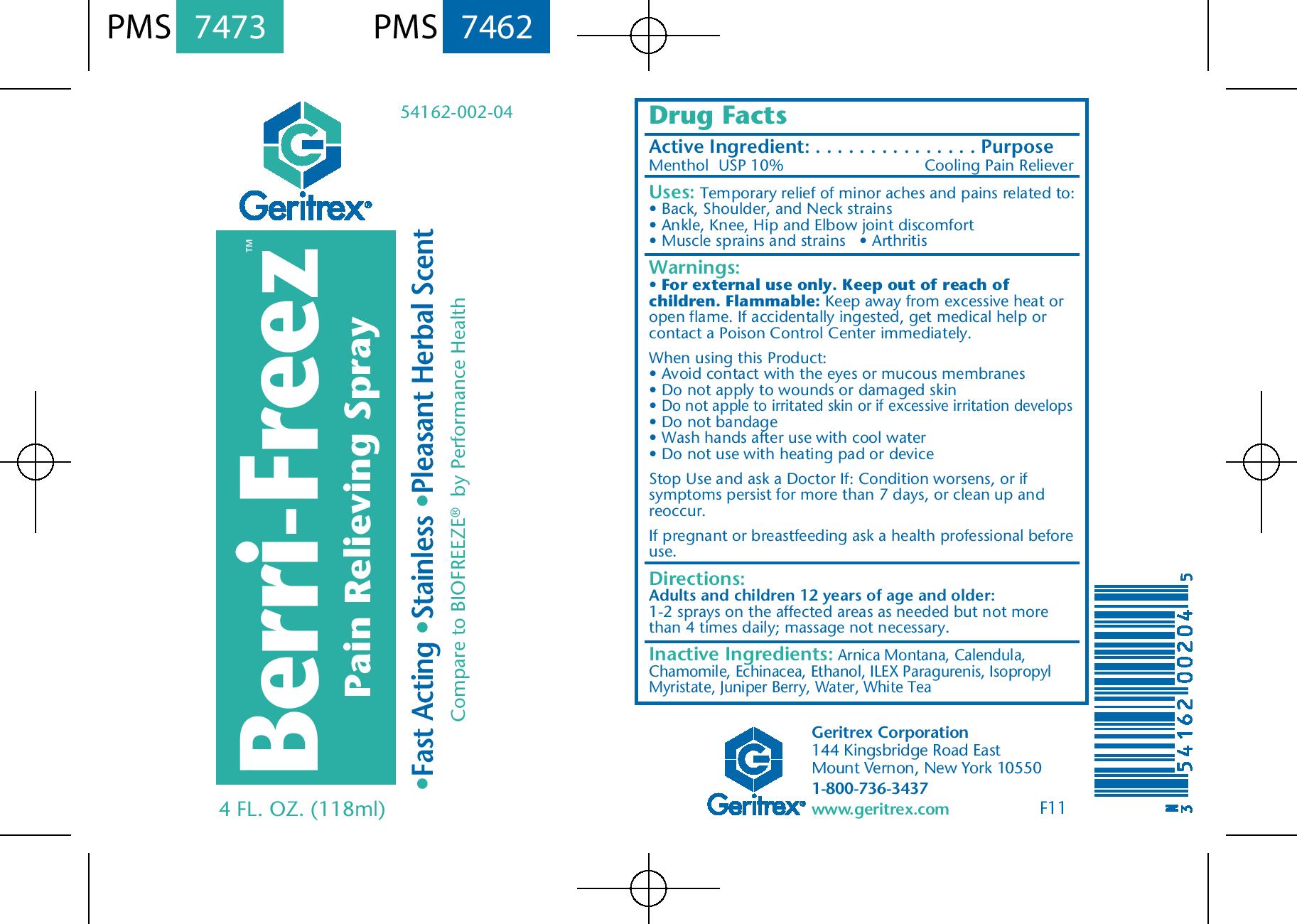 DRUG LABEL: Berri-Freez
NDC: 54162-002 | Form: SPRAY
Manufacturer: Geritrex LLC
Category: otc | Type: HUMAN OTC DRUG LABEL
Date: 20160812

ACTIVE INGREDIENTS: MENTHOL 11.8 g/118 mL
INACTIVE INGREDIENTS: ARNICA MONTANA; CALENDULA OFFICINALIS FLOWER; ECHINACEA, UNSPECIFIED; CHAMOMILE; WHITE TEA; ALCOHOL; ILEX PARAGUARIENSIS LEAF; ISOPROPYL MYRISTATE; JUNIPER BERRY; WATER

Berri-Freez

Active Ingredient:

Menthol USP 10%

Purpose:

Cooling Pain Reliever

Uses:

Temporary relief of minor aches and pains related to:

- Back, Shoulder, and Neck strains
- Ankle, Knee, Hip and Elbow joint discomfort
- Muscle sprains and strains
- Arthritis

Warnings:

For external use only. Keep out of reach of children.

WARNINGS

Flammable: Keep away from excessive heat or open flame. If accidnetally ingested, get medical help or contact a Poison Control Center immediately.

When using this Product:

Avoid contact with the eyes or mucous membranes

Do not apply to wounds or damaged skin

Do not apply to irritated skin or if excessive irritation develops

Do not bandage

Wash hands after use with cool water

Do not use with heating pad or device

Stop Use and ask a Doctor if: Condition worsens, or if symptoms persist for more than 7 days, or clear up or reoccur

PREGNANCY OR BREAST FEEDING

If pregnant or breastfeeding ask a health professional before use.

DOSAGE AND ADMINISTRATION

Adults and children 12 years of age and older:
1-2 sprays on the affected areas as needed but not more than 4 times daily; massage not necessary.

Inactive Ingredients:

Arnica Montana, Calendula, Chamomile, Echinacea, Ethanol, ILEX Paragurenis, Isopropyl Myristate, Juniper Berry, Water, White Tea